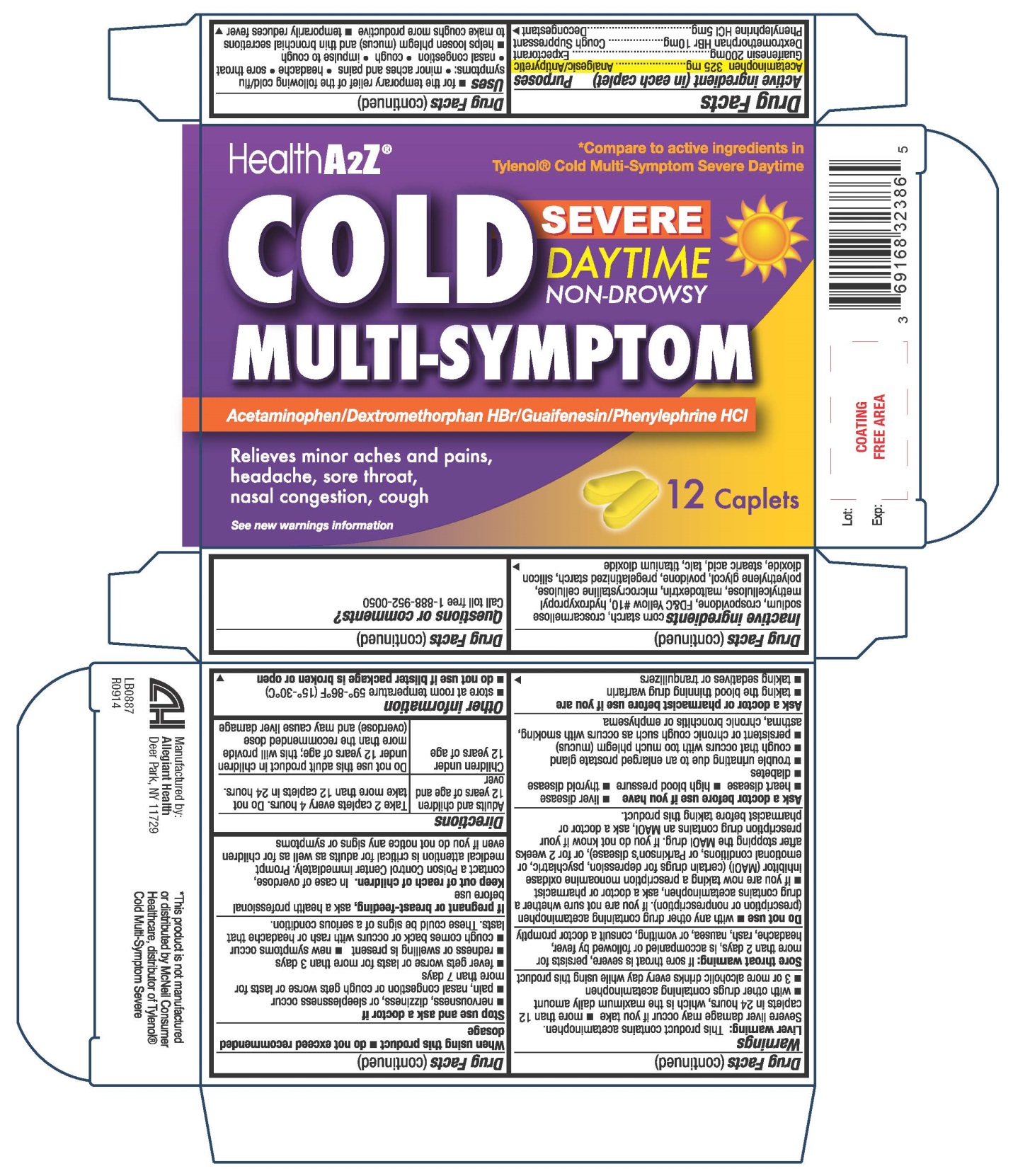 DRUG LABEL: Cold Multi-Symptom
NDC: 69168-323 | Form: TABLET
Manufacturer: Allegiant Health
Category: otc | Type: HUMAN OTC DRUG LABEL
Date: 20141223

ACTIVE INGREDIENTS: ACETAMINOPHEN 325 mg/1 1; GUAIFENESIN 200 mg/1 1; DEXTROMETHORPHAN HYDROBROMIDE 10 mg/1 1; PHENYLEPHRINE HYDROCHLORIDE 5 mg/1 1
INACTIVE INGREDIENTS: STARCH, CORN; CROSCARMELLOSE SODIUM; D&C YELLOW NO. 10; HYPROMELLOSES; SILICON DIOXIDE; CELLULOSE, MICROCRYSTALLINE; POVIDONES; STEARIC ACID; TITANIUM DIOXIDE; CROSPOVIDONE; MALTODEXTRIN; POLYETHYLENE GLYCOLS

Drug Facts

Active ingredient

Acetaminophen 325 mg
Guaifenesin 200 mg
Dextromethorphan HBr 10 mg
Phenylephrine HCI 5 mg

Purpose

Analgesic/Antipyretic
Expectorant
Cough suppressant
Decongestant

Uses

for the temporary relief of the following cold/flu symptoms: •minor aches and pains • headache • sore throat •nasal congestion •cough •impulse to cough helps loosen phlegm (mucus) and thin bronchial secretions to make coughs more productive temporarily reduces fever

Warnings

Liver warning

This product contains acetaminophen. Severe liver damage may occur if you take more than 12 caplets in 24 hours, which is the maximum daily amount with other drugs containing acetaminophen 3 or more alcoholic drinks every day while using this product

Sore throat warning

If sore throat is severe, persists for more than 2 days, is accompanied or followed by fever, headache, rash, nausea, or vomiting, consult a doctor promptly.

Do Not Use

with any other products containing acetaminophen (prescription or nonprescription). If you are not
sure whether a drug contains acetaminophen, ask a doctor or pharmacistif you are now taking a prescription monoamine oxidase inhibitor (MAOI) (certain drugs for depression, psychiatric or emotional conditions, or Parkinson’s disease), or for 2 weeks after stopping the MAOI drugs. If you do not know if your prescription drug contains an MAOI, ask a doctor or pharmacist before taking this product

Ask a doctor before use if you have

liver disease■ heart disease■ high blood pressure ■ thyroid disease ■ diabetes ■ trouble urinating
due to an enlarged prostate gland ■ cough that occurs with too much phlegm (mucus) ■ persistent or chronic cough such as occurs with smoking, asthma, chronic bronchitis or emphysema

Ask a doctor or pharmacist before use if you are

taking the blood thinning drug warfarin taking sedatives or tranquilizers

When using this product

do not use exceed recommended dosage

Stop use and ask a doctor if

■ nervousness, dizziness, or sleeplessness occur ■ pain, nasal congestion or cough gets worse or lasts for more than 7 days ■ fever gets worse or lasts for more than 3 days ■ redness or swelling is present ■ new symptoms occur ■ cough comes back or occurs with rash or headache that lasts. These could be signs of a serious condition.

If pregnant or breast-feeding

ask a health professional before use

Keep Out of Reach of Children

In case of overdose, contact a Poison Control Center immediately. Prompt medical attention is critical for adults as well as for children even if you do not notice any signs or symptoms

Directions

Adults and children 12 years and over: take 2 caplets every 4 hours ■ do not take more than a total of 12 caplets in 24 hours
Children under 12 years: Do not use this adult product in children under 12 years of age. This will provide more than recommended dose (overdose) and may cause liver damage

Other Information

store at room temperature 59°-86° F (15°-30° C) do not use if blister is torn or open

Inactive Ingredients

corn starch, croscarmellose sodium, crospovidone, FD&C Yellow #10, hydroxypropyl methylcellulose, maltodextrin, microcrystalline cellulose, polyethylene glycol, povidone, pregelatinized starch, silicon dioxide, stearic acid, talc, titanium dioxide

Questions or comments?

Call toll free 1-888-952-0050